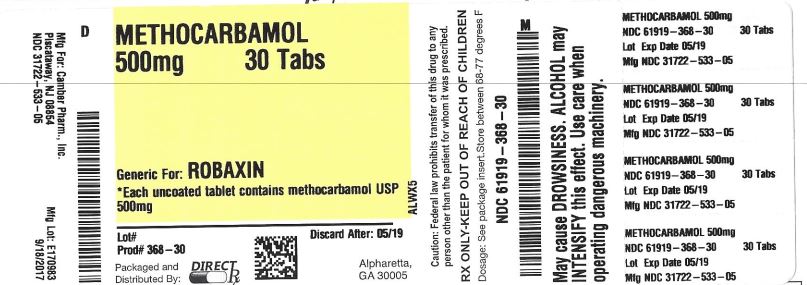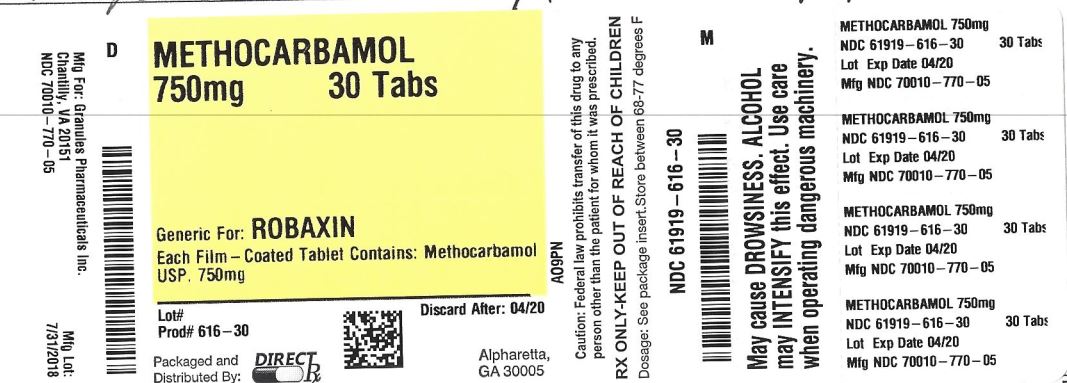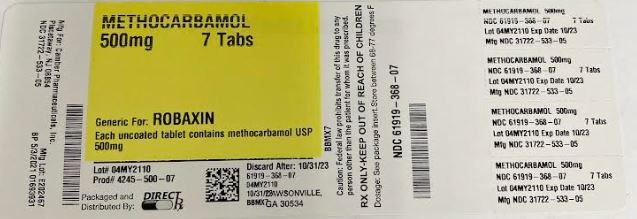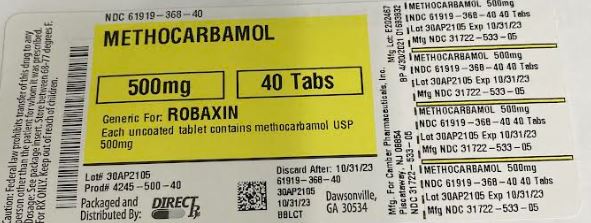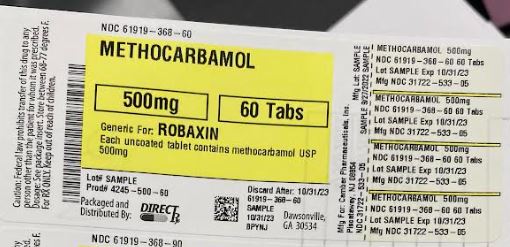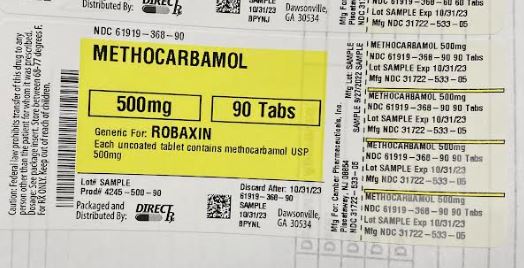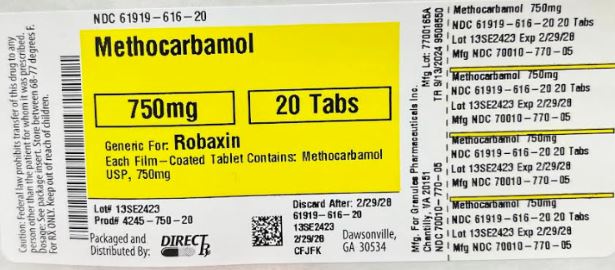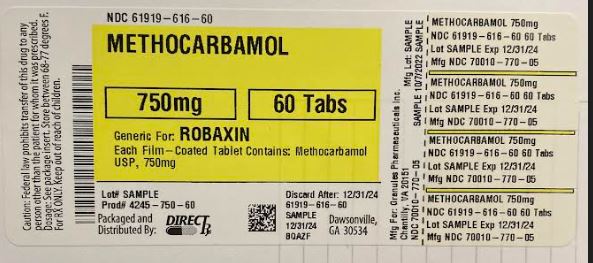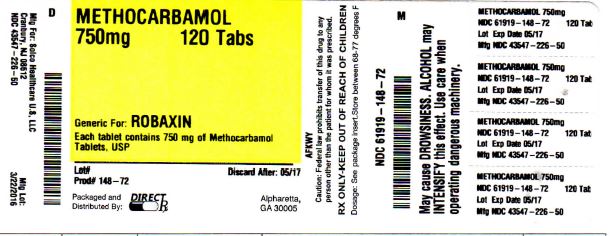 DRUG LABEL: Methocarbamol
NDC: 61919-616 | Form: TABLET, COATED
Manufacturer: DIRECT RX
Category: prescription | Type: HUMAN PRESCRIPTION DRUG LABEL
Date: 20260108

ACTIVE INGREDIENTS: METHOCARBAMOL 750 mg/1 1
INACTIVE INGREDIENTS: STEARIC ACID; FD&C YELLOW NO. 6; HYPROMELLOSE 2910 (6 MPA.S); POLYSORBATE 80; TITANIUM DIOXIDE; SILICON DIOXIDE; SODIUM LAURYL SULFATE; HYDROXYPROPYL CELLULOSE (1600000 WAMW); PROPYLENE GLYCOL; STARCH, CORN; POVIDONE; SODIUM STARCH GLYCOLATE TYPE A POTATO

METHOCARBAMOL 750mg 120TABS

DESCRIPTION

Methocarbamol tablets, USP, a carbamate derivative of guaifenesin, are a central nervous system (CNS) depressant with sedative and musculoskeletal relaxant properties.

The chemical name of methocarbamol is 3-(2-meth-oxyphenoxy)-1,2-propanediol 1-carbamate and has the empirical formula C11H15NO5. Its molecular weight is 241.24. The structural formula is shown below.

[Methocarbamol Chemical Structure]

Methocarbamol is a white powder, sparingly soluble in water and chloroform, soluble in alcohol (only with heating) and propylene glycol, and insoluble in benzene and n-hexane.

Methocarbamol tablets, USP are available as 500 mg and 750 mg tablets for oral administration. Methocarbamol tablets, USP 500 mg and 750 mg contain the following inactive ingredients: povidone, sodium starch glycolate and magnesium stearate.

CLINICAL PHARMACOLOGY

The mechanism of action of methocarbamol in humans has not been established, but may be due to general central nervous system (CNS) depression. It has no direct action on the contractile mechanism of striated muscle, the motor end plate or the nerve fiber.

Pharmacokinetics

In healthy volunteers, the plasma clearance of methocarbamol ranges between 0.20 and 0.80 L/h/kg, the mean plasma elimination half-life ranges between 1 and 2 hours, and the plasma protein binding ranges between 46% and 50%.

Methocarbamol is metabolized via dealkylation and hydroxylation. Conjugation of methocarbamol also is likely. Essentially all methocarbamol metabolites are eliminated in the urine. Small amounts of unchanged methocarbamol also are excreted in the urine.

INDICATIONS AND USAGE

Methocarbamol tablets, USP are indicated as an adjunct to rest, physical therapy, and other measures for the relief of discomfort associated with acute, painful musculoskeletal conditions. The mode of action of methocarbamol has not been clearly identified, but may be related to its sedative properties. Methocarbamol does not directly relax tense skeletal muscles in man.

CONTRAINDICATIONS

Methocarbamol tablets, USP are contraindicated in patients hypersensitive to methocarbamol or to any of the tablet components.

WARNINGS

Since methocarbamol may possess a general CNS depressant effect, patients receiving Methocarbamol tablets, USP should be cautioned about combined effects with alcohol and other CNS depressants.

Safe use of Methocarbamol tablets, USP has not been established with regard to possible adverse effects upon fetal development. There have been reports of fetal and congenital abnormalities following in utero exposure to methocarbamol. Therefore, Methocarbamol tablets, USP should not be used in women who are or may become pregnant and particularly during early pregnancy unless in the judgment of the physician the potential benefits outweigh the possible hazards (see Precautions, Pregnancy).

Use In Activities Requiring Mental Alertness

Methocarbamol may impair mental and/or physical abilities required for performance of hazardous tasks, such as operating machinery or driving a motor vehicle. Patients should be cautioned about operating machinery, including automobiles, until they are reasonably certain that methocarbamol therapy does not adversely affect their ability to engage in such activities

PRECAUTIONS

Information for patients

Patients should be cautioned that methocarbamol may cause drowsiness or dizziness, which may impair their ability to operate motor vehicles or machinery.

Because methocarbamol may possess a general CNS-depressant effect, patients should be cautioned about combined effects with alcohol and other CNS depressants.

Drug interactions

See Warnings and Precautions for interaction with CNS drugs and alcohol.

Methocarbamol may inhibit the effect of pyridostigmine bromide. Therefore, methocarbamol should be used with caution in patients with myasthenia gravis receiving anticholinesterase agents.

Drug/laboratory test interactions

Methocarbamol may cause a color interference in certain screening tests for 5-hydroxyindoleacetic acid (5-HIAA) using nitrosonaphthol reagent and in screening tests for urinary vanillylmandelic acid (VMA) using the Gitlow method.

Carcinogenesis, mutagenesis, impairment of fertility

Long-term studies to evaluate the carcinogenic potential of methocarbamol have not been performed. No studies have been conducted to assess the effect of methocarbamol on mutagenesis or its potential to impair fertility.

Pregnancy

Teratogenic effects

Pregnancy Category C

Animal reproduction studies have not been conducted with methocarbamol. It is also not known whether methocarbamol can cause fetal harm when administered to a pregnant woman or can affect reproduction capacity. Methocarbamol tablets, USP should be given to a pregnant woman only if clearly needed.

Safe use of Methocarbamol tablets, USP has not been established with regard to possible adverse effects upon fetal development. There have been reports of fetal and congenital abnormalities following in utero exposure to methocarbamol. Therefore, Methocarbamol tablets, USP should not be used in women who are or may become pregnant and particularly during early pregnancy unless in the judgment of the physician the potential benefits outweigh the possible hazards (see Warnings).

Nursing mothers

Methocarbamol and/or its metabolites are excreted in the milk of dogs; however, it is not known whether methocarbamol or its metabolites are excreted in human milk. Because many drugs are excreted in human milk, caution should be exercised when Methocarbamol tablets, USP are administered to a nursing woman.

Pediatric use

Safety and effectiveness of Methocarbamol tablets, USP in pediatric patients below the age of 16 have not been established.

ADVERSE REACTIONS

Adverse reactions reported coincident with the administration of methocarbamol include:

Body as a whole:

Anaphylactic reaction, angioneurotic edema, fever, headache

Cardiovascular system:

Bradycardia, flushing, hypotension, syncope, thrombophlebitis

Digestive system:

Dyspepsia, jaundice (including cholestatic jaundice), nausea and vomiting

Hemic and lymphatic system:

Leukopenia

Immune system:

Hypersensitivity reactions

Nervous system:

Amnesia, confusion, diplopia, dizziness or lightheadedness, drowsiness, insomnia, mild muscular incoordination, nystagmus, sedation, seizures (including grand mal), vertigo

Skin and special senses:

Blurred vision, conjunctivitis, nasal congestion, metallic taste, pruritus, rash, urticaria

OVERDOSAGE

Limited information is available on the acute toxicity of methocarbamol. Overdose of methocarbamol is frequently in conjunction with alcohol or other CNS depressants and includes the following symptoms: nausea, drowsiness, blurred vision, hypotension, seizures, and coma.

In post-marketing experience, deaths have been reported with an overdose of methocarbamol alone or in the presence of other CNS depressants, alcohol or psychotropic drugs.

Treatment

Management of overdose includes symptomatic and supportive treatment. Supportive measures include maintenance of an adequate airway, monitoring urinary output and vital signs, and administration of intravenous fluids if necessary. The usefulness of hemodialysis in managing overdose is unknown.

DOSAGE AND ADMINISTRATION

Methocarbamol tablets, USP, 500 mg – Adults:

Initial dosage: 3 tablets q.i.d.

Maintenance dosage: 2 tablets q.i.d.

Methocarbamol tablets, USP: 750 mg – Adults:

Initial dosage: 2 tablets q.i.d.

Maintenance dosage: 1 tablet q.4h. or 2 tablets t.i.d.

Six grams a day are recommended for the first 48 to 72 hours of treatment. (For severe conditions 8 grams a day may be administered). Thereafter, the dosage can usually be reduced to approximately 4 grams a day.

STORAGE

Store at controlled room temperature, between 20°C and 25°C (68°F and 77°F).
[see USP Controlled Room Temperature].
Dispense in tight container.

HOW SUPPLIED

Methocarbamol tablets, USP 500 mg are white to off white, capsule shaped, tablets debossed with ‘H’ on scored side and ‘114’ on unscored side .

Methocarbamol tablets, USP 750 mg are light orange colored, capletshaped film coated tablets debossed with "G" on one side and"750" on other side.

Store between 20ºC and 25ºC (68ºF and 77º F)

[see USP Controlled Room Temperature].

Dispense in tight container.

Manufactured for:

Granules USA, Inc.

Parsippany, NJ 07054

Toll-free: 1-877-770-3183

Manufactured by:

Granules India Limited

Hyderabad-500 081

Made in India

Issued: January 2017